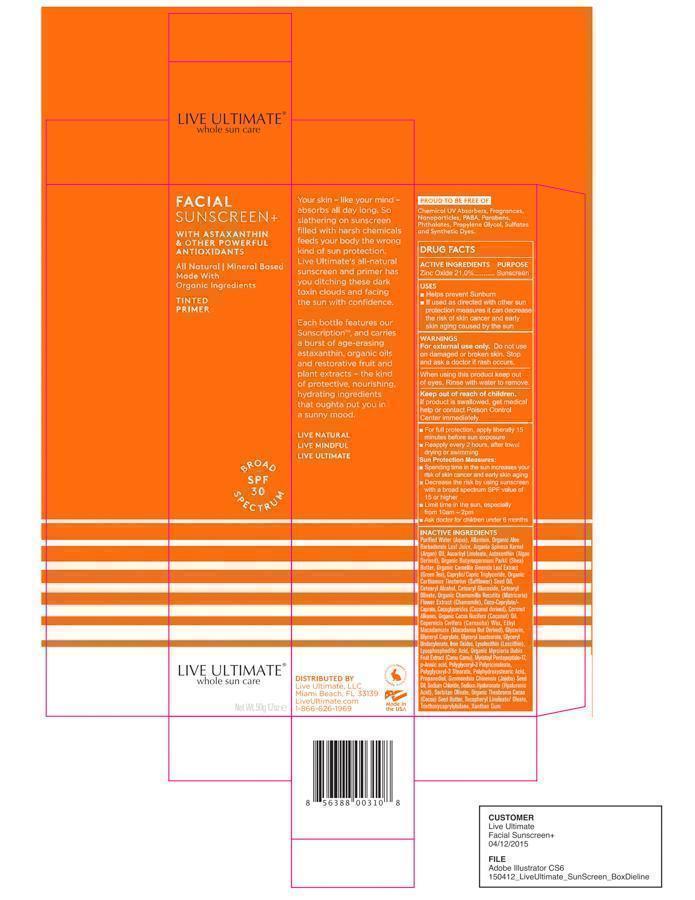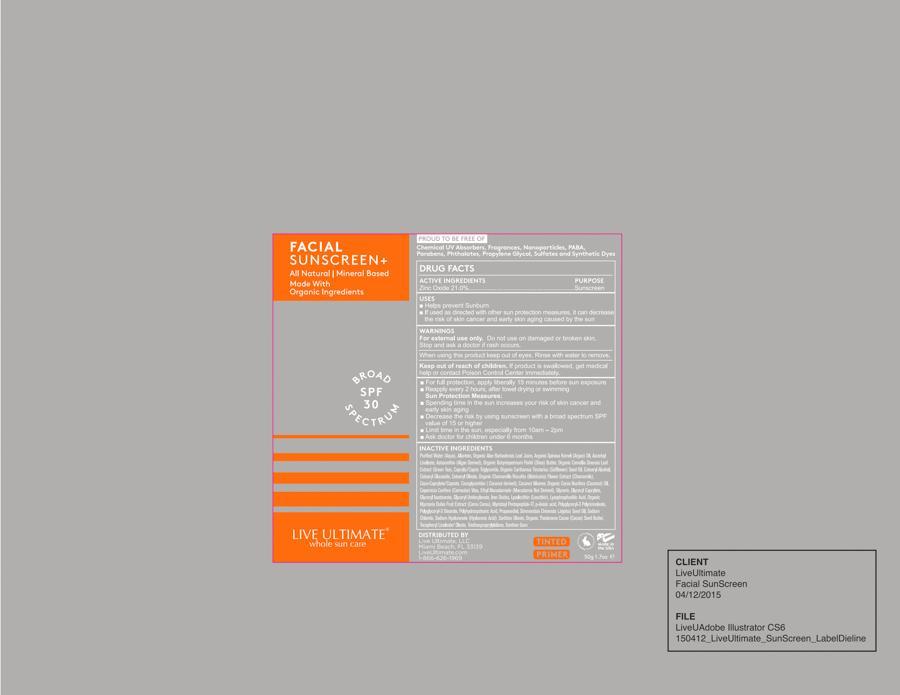 DRUG LABEL: Live Ultimate Facial Sunscreen SPF30
NDC: 59958-230 | Form: CREAM
Manufacturer: Owen Biosciences Inc
Category: otc | Type: HUMAN OTC DRUG LABEL
Date: 20241105

ACTIVE INGREDIENTS: ZINC OXIDE 21 g/100 g
INACTIVE INGREDIENTS: WATER 34 g/100 g; ETHYL MACADAMIATE 5 1/100 g; GLYCERIN 5 1/100 g; PROPANEDIOL 5 1/100 g; POLYGLYCERYL-3 RICINOLEATE 4 1/100 g; JOJOBA OIL 15 1/100 g

Live Ultimate Facial Sunscreen SPF30

Drug Facts

Active ingredients Purpose

Zinc Oxide 21.0% Sunscreen

USES

- Helps prevent Sunburn
- If used as directed with other sun protection measures it can decrease the risk of skin cancer and early skin aging caused by the sun

Warnings

For external use only. Do not use on damaged or broken skin. Stop and ask a doctor if rash occurs.

When using this product keep out of eyes. Rinse with water to remove.

Keep out of reach of children If product is swallowed, get medical help or contact Poison Control Center immdeiately.

INDICATIONS AND USAGE

- For full protection, apply liberally 15 minutes before sun exposure
- Reapply every 2 hours, after towel drying or swimming

Sun Protection Measures:

- Spending time in the sun increases your risk of skin cancer and early skin aging
- Decrease the risk by using sunscreen with a broad spectrum SPF calue of 15 or higher
- Limit time in the sun, especially from 10am - 2pm
- Ask doctor for children under 6 months

Inactive Ingredients

Purified Water (Aqua), Allantoin, Organic Aloe Barbadenis Leaf Juice, Argania Spinosa Kernel (Argan) Oil, Ascorbyl Linoleate, Astaxanthin (Algae Derived), Organic Butyrospermum Parkii (Shea) Butter, Organic Camellia Sinensis Leaf Extract (Green Tea), Caprylic/Capric Triglyceride, Organic Carthamus tinctoris (Safflower) Seed Oil, Cetearyl Alcohol, Vetearyl Glucoside, Cetearyl Olivate, Organic Chamomilla Recutita (Matricaria) Flower Extract (Chamomile), Coco-Caprylate/-Caprate Cocoglycerides (Coconut derived), Coconut Alkanes, Organic Cocos Nucifera (Coconut) Oil, Copernicia Cerifera (Carnauba) Wax, Ethyl Macadamiate (Macadamia Nut Derived), Glycerin, Glyceryl Caprylate, Glyceryl Isostearate, Glyceryl Undecylenate, Iron Oxides, Lysolecithin (Lescithin), Lysophosphaditic Acid, Organic Myrciara Dubia Fruit Extract (Camu Camu), Myristoyl Pentapeptide-17, p-Anisicacid, Polyglyceryl-3 Polyhdroxystearic Acid, Propanediol, Simmondsia Chinensis (Jojoba) Seed Oil, Sodium Chloride, Sodium Hyaluronate (Hyaluronic Acid), Sorbitan Olivate, Organic Theobroma Cacao (Cocoa) Seed Butter, Tocopheryl Linoleate/Oleate, Triethoxycaprylylsilane, Xanthan Gum

Directions

For full protection, apply liberally 15 minutes before sun exposure
Reapply every 2 hours, after towel drying or swimming

Sun Protection Measures:

Spending time in the sun increases your risk of skin cancer and early skin aging
Decrease the risk by using sunscreen with a broad spectrum SPF calue of 15 or higher
Limit time in the sun, especially from 10am - 2pm
Ask doctor for children under 6 months

RECENT MAJOR CHANGES

For full protection, apply liberally 15 minutes before sun exposure
Reapply every 2 hours, after towel drying or swimming

Sun Protection Measures:

Spending time in the sun increases your risk of skin cancer and early skin aging
Decrease the risk by using sunscreen with a broad spectrum SPF calue of 15 or higher
Limit time in the sun, especially from 10am - 2pm
Ask doctor for children under 6 months

Keep out of reach of children If product is swallowed, get medical help or contact Poison Control Center immdeiately.

PACKAGE LABEL

box.jpg

label.jpg